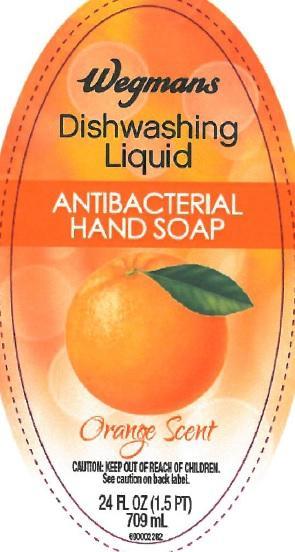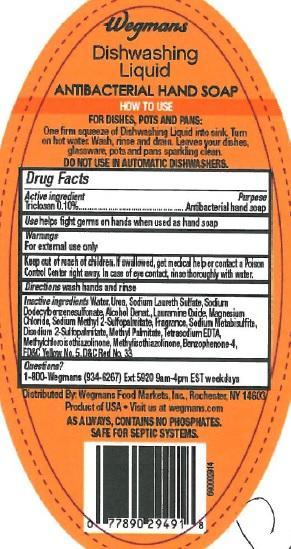 DRUG LABEL: Wegmans Orange Scent
NDC: 63691-026 | Form: SOAP
Manufacturer: Sun Products Corporation
Category: otc | Type: HUMAN OTC DRUG LABEL
Date: 20141231

ACTIVE INGREDIENTS: TRICLOSAN 0.1 g/100 mL
INACTIVE INGREDIENTS: WATER; UREA; SODIUM LAURETH SULFATE; SODIUM DODECYLBENZENESULFONATE; ALCOHOL; LAURAMINE OXIDE; MAGNESIUM CHLORIDE; SODIUM METABISULFITE; DISODIUM 2-SULFOPALMITATE; METHYL PALMITATE; EDETATE SODIUM; METHYLCHLOROISOTHIAZOLINONE; METHYLISOTHIAZOLINONE; SULISOBENZONE; FD&C YELLOW NO. 5; D&C RED NO. 33

Active ingredient

Triclosan 0.10%

INDICATIONS AND USAGE

Use helps fight germs on hands when used as a hand soap

WARNINGS

For external use only

Keep out of reach of children. If swallowed, get medical help or contact a Poison Control Center right away. In case of eye contact, rinse thoroughly with water.

DOSAGE AND ADMINISTRATION

Directions wash hands and rinse

PURPOSE

Antibacterial hand soap

INACTIVE INGREDIENT

Inactive ingredients Water, Urea, Sodium Laureth Sulfate, Sodium Dodecylbenzenesulfonate, Alcohol Denat., Lauramine Oxide, Magnesium Chloride, Sodium Methyl 2-Sulfopalmitate, Fragrance, Sodium Metabisulfite, Disodium 2-Sulfopalmitate, Methyl Palmitate, Tetrasodium EDTA, Methylchloroisothiazolinone, Methylisothiazolinone, Benzophenone-4, FD&C Yellow No. 5, D&C Red No. 33

QUESTIONS

Questions? 1-800-Wegmans (934-6267) Ext 5920 9am-4pm EST workdays

PACKAGE LABEL

LBLFR

LBLBK